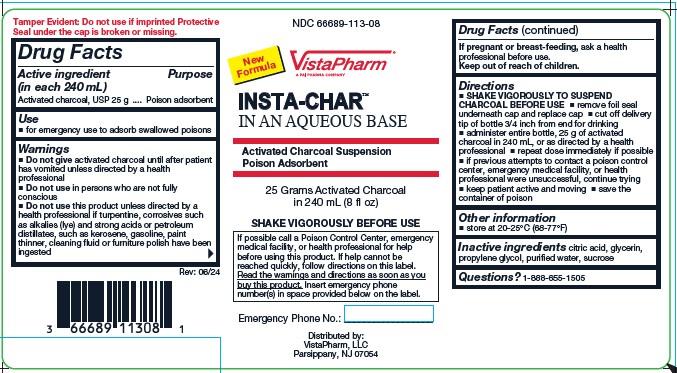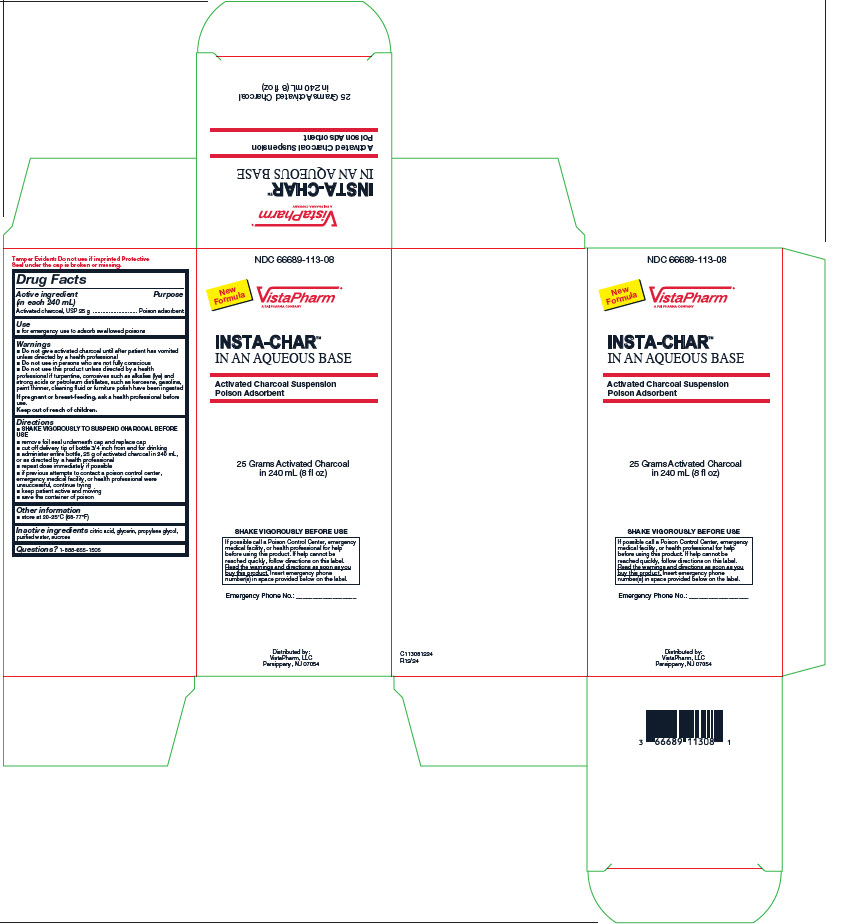 DRUG LABEL: INSTA-CHAR AQUEOUS
NDC: 66689-113 | Form: SUSPENSION
Manufacturer: VistaPharm, LLC
Category: otc | Type: HUMAN OTC DRUG LABEL
Date: 20250116

ACTIVE INGREDIENTS: ACTIVATED CHARCOAL 25 g/240 mL
INACTIVE INGREDIENTS: ANHYDROUS CITRIC ACID; GLYCERIN; PROPYLENE GLYCOL; WATER; SUCROSE

INSTA-CHAR AQUEOUS

Active ingredient (in each 240 mL)

Activated charcoal, USP 25 g

Purpose

Poison adsorbent

Use

- for emergency use to adsorb swallowed poisons

Warnings

- Do not give activated charcoal until after patient has vomited unless directed by a health professional
- Do not use in persons who are not fully conscious
- Do not use this product unless directed by a health professional if turpentine, corrosives such as alkalies (lye) and strong acids or petroleum distillates, such as kerosene, gasoline, paint thinner, cleaning fluid or furniture polish have been ingested

If pregnant or breast-feeding,

ask a health professional before use.

Directions

- SHAKE VIGOROUSLY TO SUSPEND CHARCOAL BEFORE USE
- remove foil seal underneath cap and replace cap
- cut off delivery tip of bottle 3/4 inch from end for drinking
- administer entire bottle, 25 g of activated charcoal in 240 mL, or as directed by a health professional
- repeat dose immediately, if possible
- if previous attempts to contact a poison control center, emergency medical facility, or health professional were unsuccessful, continue trying
- keep patient active and moving
- save the container of poison

Other information

- store at 20-25ºC (68-77ºF)

Inactive Ingredients

citric acid, glycerin, propylene glycol, purified water, sucrose

Questions?

1-888-655-1505

PRINCIPAL DISPLAY PANEL-LABEL

NDC 66689-113-08

INSTA-CHAR™
IN AN AQUEOUS BASE
Activated Charcoal Suspension
Poison Adsorbent

Distributed by:
VistaPharm Inc.
Parsippany, NJ 07054

PRINCIPAL DISPLAY PANEL-CARTON

NDC 66689-113-08

INSTA-CHAR™
IN AN AQUEOUS BASE

Activated Charcoal Suspension
Poison Adsorbet

Distributed by:

VistaPharm, LLC
Parsippany, NJ 07054